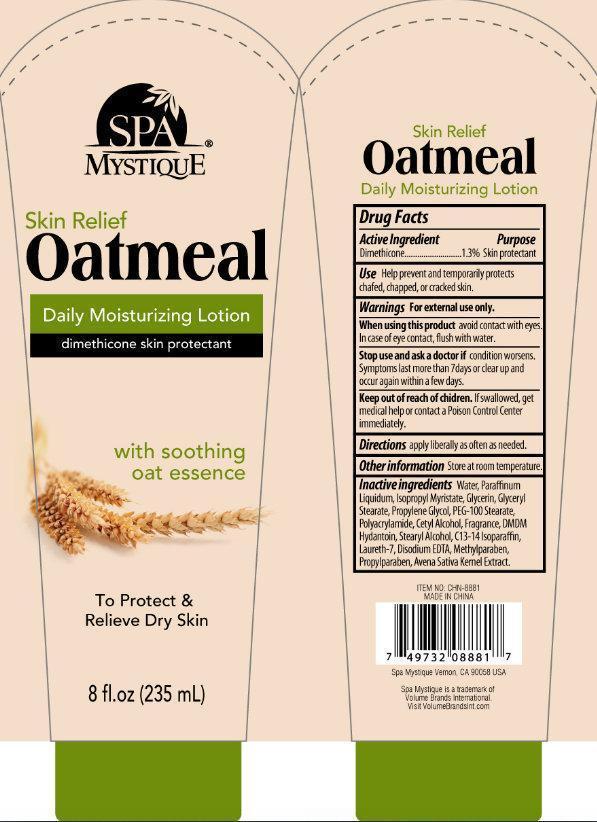 DRUG LABEL: SPA MYSTIQUE SKIN RELIEF OATMEAL DAILY MOISTURIZING
NDC: 50523-100 | Form: LOTION
Manufacturer: Volume Distributors, Inc.
Category: otc | Type: HUMAN OTC DRUG LABEL
Date: 20140804

ACTIVE INGREDIENTS: DIMETHICONE 13 mg/1 mL
INACTIVE INGREDIENTS: WATER; ISOPROPYL MYRISTATE; GLYCERIN; GLYCERYL MONOSTEARATE; PROPYLENE GLYCOL; PEG-100 STEARATE; POLYQUATERNIUM-7 (70/30 ACRYLAMIDE/DADMAC; 1600000 MW); CETYL ALCOHOL; DMDM HYDANTOIN; STEARYL ALCOHOL; C13-14 ISOPARAFFIN; LAURETH-7; EDETATE DISODIUM; METHYLPARABEN; PROPYLPARABEN; OAT; MINERAL OIL

SPA MYSTIQUE SKIN RELIEF OATMEAL DAILY MOISTURIZING LOTION

Active Ingredient

Dimethicone.............1.3%

Purpose

Skin protectant

Use

Help prevent and temporarily protects chafed, chapped, or cracked skin.

Warnings

For external use only.

When using this product

avoid contact with eyes. In case of eye contact, flush with water.

Stop use and ask a doctor if

condition worsens. Symptoms last more than 7 days or clear up and occur again within a few days.

Keep out of reach of children.

If swallowed, get medical help or contact a Poison Control Center immediately.

Directions

apply liberally as often as needed.

Other information

Store at room temperature.

Inactive ingredients

Water, Paraffinum Liquidum, Isopropyl Myristate, Glycerin, Glyceryl Stearate, Propylene Glycol, PEG-100 Stearate, Polyacrylamide, Cetyl Alcohol, Fragrance, DMDM Hydantoin, STearyl Alcohol, C13-14 Isoparaffin, Laureth-7, Disodium EDTA, Methylparaben, Propylparaben, Avena Sativa Kernel Extract.

PACKAGE LABEL

SPA MYSTIQUE Skin Relief Oatmeal Daily Moisturizing Lotion dimethicone skin protectant with soothing oat essence To protect and Relieve Dry Skin 8 fl. oz (235 mL) MADE IN CHINA Spa Mystique Vernon, CA 90058 USA Spa Mystique is a trademark of Volume Brands International Vist VolumeBrandIint.com